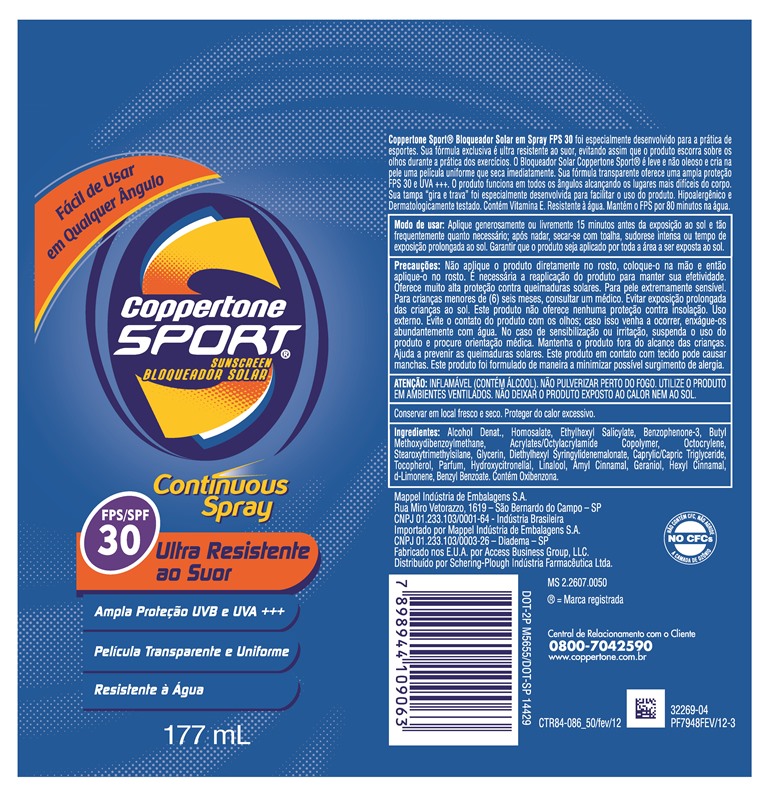 DRUG LABEL: coppertone sport
NDC: 11523-7382 | Form: SPRAY
Manufacturer: Bayer HealthCare LLC.
Category: otc | Type: HUMAN OTC DRUG LABEL
Date: 20200120

ACTIVE INGREDIENTS: OXYBENZONE 34.35 mg/1 mL; OCTOCRYLENE 17.18 mg/1 mL; OCTISALATE 39.08 mg/1 mL; AVOBENZONE 25.76 mg/1 mL; HOMOSALATE 85.88 mg/1 mL
INACTIVE INGREDIENTS: ALCOHOL; STEAROXYTRIMETHYLSILANE; DIETHYLHEXYL SYRINGYLIDENEMALONATE; TOCOPHEROL; GLYCERIN

Coppertone Sport Continuous Spray Sunscreen SPF 30

ACTIVE INGREDIENT

each 1mL contains:

Avobenzone 25.76mg

Homosalate 85.88 mg

Octisalate 39.08 mg

Octocrylene 17.18mg

Oxybenzone 34.35mg